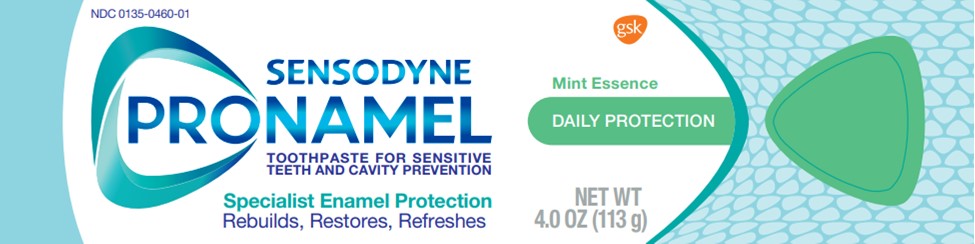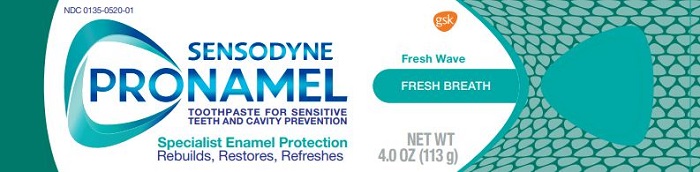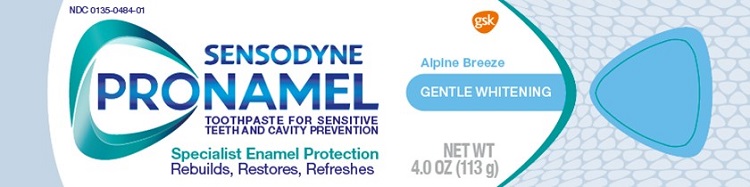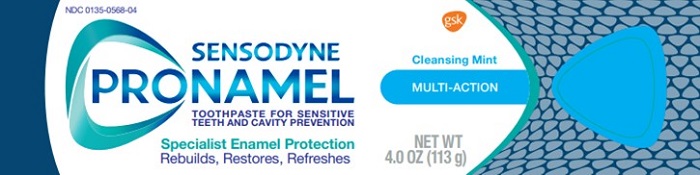 DRUG LABEL: SENSODYNE PRONAMEL

NDC: 0135-0484 | Form: PASTE
Manufacturer: Haleon US Holdings LLC
Category: otc | Type: HUMAN OTC DRUG LABEL
Date: 20240124

ACTIVE INGREDIENTS: POTASSIUM NITRATE 50 mg/1 g; SODIUM FLUORIDE 1.15 mg/1 g
INACTIVE INGREDIENTS: WATER; SORBITOL; HYDRATED SILICA; GLYCERIN; POLYETHYLENE GLYCOL 400; COCAMIDOPROPYL BETAINE; TITANIUM DIOXIDE; XANTHAN GUM; SACCHARIN SODIUM; SODIUM HYDROXIDE

Drug Facts

Active ingredients

Potassium nitrate 5%

Sodium fluoride 0.25% (0.15% w/v fluoride ion)

Purpose

Antihypersensitivity

Anticavity

Uses

- builds increasing protection against painful sensitivity of the teeth to cold, heat, acids, sweets, or contact.
- aids in the prevention of dental cavities.

Warnings

Stop use and ask a dentist if

- the problem persists or worsens. Sensitive teeth may indicate a serious problem that may need prompt care by a dentist.
- pain/sensitivity still persists after 4 weeks of use.

Keep out of reach of children.

If more than used for brushing is accidentally swallowed, get medical help or contact a Poison Control Center right away.

Directions

- adults and children 12 years of age and older:
  - apply at least a 1-inch strip of the product onto a soft bristle toothbrush.
  - brush teeth thoroughly for at least 1 minute twice a day (morning and evening), and not more than 3 times a day, or as recommended by a dentist or doctor. Make sure to brush all sensitive areas of the teeth. Minimize swallowing. Spit out after brushing.
- children under 12 years of age:Consult a dentist or doctor.

Other information (Gentle Whitening, Daily Protection, Fresh Breath, Multi-Action)

- do not store above 30°C (86°F)

Inactive ingredients (Gentle Whitening)

water, sorbitol, hydrated silica, glycerin, PEG-8, cocamidopropyl betaine, flavor, titanium dioxide, xanthan gum, sodium saccharin, sodium hydroxide

Inactive ingredients (Daily Protection)

water, sorbitol, hydrated silica, glycerin, PEG-8, cocamidopropyl betaine, flavor, xanthan gum, sodium saccharin, titanium dioxide, sodium hydroxide

Inactive ingredients (Fresh Breath)

water, sorbitol, hydrated silica, glycerin, PEG-8, cocamidopropyl betaine, flavor, xanthan gum, sodium saccharin, titanium dioxide, sodium hydroxide

Inactive ingredients (Multi-Action)

water, sorbitol, hydrated silica, glycerin, flavor, cocamidopropyl betaine, xanthan gum, sodium saccharin, mica, titanium dioxide, sodium hydroxide

Questions or comments?

1-866-844-2797

Principal Display Panel

NDC 0135-0484-01

SENSODYNE

PRONAMEL

TOOTHPASTE FOR SENSITIVE TEETH AND CAVITY PREVENTION

Alpine Breeze

GENTLE WHITENING

Specialist Enamel Protection

Rebuilds, Restores, Refreshes

NET WT 4.0 OZ (113g)

ALWAYS FOLLOW THE LABEL

SENSODYNE PRONAMEL

Does not contain: SLS/sulfates • artificial dyes • parabens • triclosan • peroxide

Acidic foods and drinks can cause enamel loss that can lead to yellowing, dullness and sensitivity. Pronamel has a specialty formulation to help rebuild and restore acid weakened enamel, helping prevent enamel loss for strong, healthy teeth.

ACID ATTACKS ENAMEL

WEAKENING THE ENAMEL STRUCTURE

PRONAMEL REBUILDS & RESTORES ENAMEL

FOR STRONG HEALTHY TEETH

Healthy white teeth start with strong enamel.

Pronamel has a proven specialist technology that has been developed to maximize the effect of fluoride on enamel.

With twice-daily brushing,
Pronamel helps to:

- Rebuild enamel strength for strong, healthy teeth
- Protect against the effects of dietary acids
- Relieve sensitive teeth
- Freshen breath
- Protect against cavities

Recycle Carton, Tube and Cap†

Save Water Turn off tap while brushing

†Recycling facilities for this product may not exist in your area

Distributed by:

GSKConsumer Healthcare

Warren, NJ 07059

Trademarks are owned by or licensed to the GSK group of companies.

©2021 GSK group of companies or its licensor.

62000000068970 Front Carton

Principal Display Panel

NDC 0135-0460-01

SENSODYNE

PRONAMEL

TOOTHPASTE FOR SENSITIVE TEETH AND CAVITY PREVENTION

Mint Essence

DAILY PROTECTION

Specialist Enamel Protection

Rebuilds, Restores, Refreshes

NET WT 4.0 OZ (113 g)

ALWAYS FOLLOW THE LABEL

SENSODYNE PRONAMEL

Does not contain: SLS/sulfates • artificial dyes • parabens • triclosan • peroxide

Acidic foods and drinks can cause enamel loss that can lead to yellowing, dullness and sensitivity. Pronamel has a specialty formulation to help rebuild and restore acid weakened enamel, helping prevent enamel loss for strong, healthy teeth.

ACID ATTACKS ENAMEL

WEAKENING THE ENAMEL STRUCTURE

PRONAMEL REBUILDS & RESTORES ENAMEL

FOR STRONG HEALTHY TEETH

Healthy white teeth start with strong enamel.

Pronamel has a proven specialist technology that has been developed to maximize the effect of fluoride on enamel.

With twice-daily brushing,
Pronamel helps to:

- Rebuild enamel strength for strong, healthy teeth
- Protect against the effects of dietary acids
- Relieve sensitive teeth
- Freshen breath
- Protect against cavities

Recycle Carton, Tube and Cap†

Save Water Turn off tap while brushing

†Recycling facilities for this product may not exist in your area

Distributed by:

GSKConsumer Healthcare

Warren, NJ 07059

Trademarks are owned by or licensed to the GSK group of companies.

©2021 GSK group of companies or its licensor.

62000000068992 Front Carton

Principal Display Panel

NDC 0135-0520-01

SENSODYNE

PRONAMEL

TOOTHPASTE FOR SENSITIVE TEETH AND CAVITY PREVENTION

Fresh Wave

FRESH BREATH

Specialist Enamel Protection

Rebuilds, Restores, Refreshes

NET WT 4.0 OZ (113 g)

ALWAYS FOLLOW THE LABEL

SENSODYNE PRONAMEL

Does not contain: SLS/sulfates • artificial dyes • parabens • triclosan • peroxide

Acidic foods and drinks can cause enamel loss that can lead to yellowing, dullness and sensitivity. Pronamel has a specialty formulation to help rebuild and restore acid weakened enamel, helping prevent enamel loss for strong, healthy teeth.

ACID ATTACKS ENAMEL

WEAKENING THE ENAMEL STRUCTURE

PRONAMEL REBUILDS & RESTORES ENAMEL

FOR STRONG HEALTHY TEETH

Healthy white teeth start with strong enamel.

Pronamel has a proven specialist technology that has been developed to maximize the effect of fluoride on enamel.

With twice-daily brushing,
Pronamel helps to:

- Rebuild enamel strength for strong, healthy teeth
- Protect against the effects of dietary acids
- Relieve sensitive teeth
- Freshen breath
- Protect against cavities

Recycle Carton, Tube and Cap†

Save Water Turn off tap while brushing

†Recycling facilities for this product may not exist in your area

Distributed by:

GSK Consumer Healthcare

Warren, NJ 07059

Trademarks are owned by or licensed to the GSK group of companies.

©2021 GSK group of companies or its licensor.

62000000068910 Front Carton

Principal Display Panel

NDC 0135-0568-04

SENSODYNE

PRONAMEL

TOOTHPASTE FOR SENSITIVE TEETH AND CAVITY PREVENTION

Cleansing Mint

MULTI-ACTION

Specialist Enamel Protection

Rebuilds, Restores, Refreshes

NET WT 4.0 OZ (113 g)

ALWAYS FOLLOW THE LABEL

SENSODYNE PRONAMEL

Does not contain: SLS/sulfates • artificial dyes • parabens • triclosan • peroxide

Acidic foods and drinks can cause enamel loss that can lead to yellowing, dullness and sensitivity. Pronamel has a specialty formulation to help rebuild and restore acid weakened enamel, helping prevent enamel loss for strong, healthy teeth.

ACID ATTACKS ENAMEL

WEAKENING THE ENAMEL STRUCTURE

PRONAMEL REBUILDS & RESTORES ENAMEL

FOR STRONG HEALTHY TEETH

Healthy white teeth start with strong enamel.

Pronamel has a proven specialist technology that has been developed to maximize the effect of fluoride on enamel.

With twice-daily brushing,
Pronamel helps to:

- Rebuild enamel strength for strong, healthy teeth
- Protect against the effects of dietary acids
- Relieve sensitive teeth
- Freshen breath
- Protect against cavities

Recycle Carton, Tube and Cap†

Save Water Turn off tap while brushing

Distributed by:

GSKConsumer Healthcare

Warren, NJ 07059

Trademarks are owned by or licensed to the GSK group of companies.

©2021 GSK group of companies or its licensor.

62000000069352 Front Carton